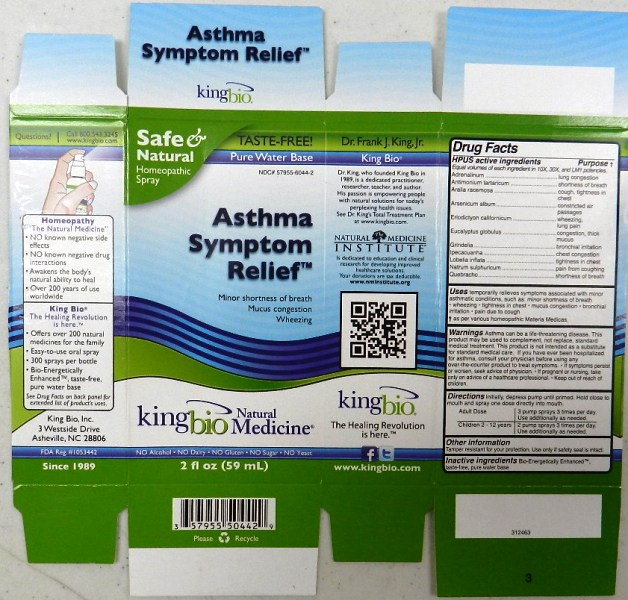 DRUG LABEL: Asthma Symptom Relief
NDC: 57955-6044 | Form: LIQUID
Manufacturer: King Bio Inc.
Category: homeopathic | Type: HUMAN OTC DRUG LABEL
Date: 20111020

ACTIVE INGREDIENTS: EPINEPHRINE 10 [hp_X]/59 mL; ANTIMONY POTASSIUM TARTRATE 10 [hp_X]/59 mL; ARALIA RACEMOSA ROOT 10 [hp_X]/59 mL; ARSENIC TRIOXIDE 10 [hp_X]/59 mL; ERIODICTYON CALIFORNICUM LEAF 10 [hp_X]/59 mL; EUCALYPTUS GLOBULUS LEAF 10 [hp_X]/59 mL; GRINDELIA HIRSUTULA FLOWERING TOP 10 [hp_X]/59 mL; IPECAC 10 [hp_X]/59 mL; LOBELIA INFLATA 10 [hp_X]/59 mL; SODIUM SULFATE 10 [hp_X]/59 mL; .BETA.-SITOSTEROL 10 [hp_X]/59 mL
INACTIVE INGREDIENTS: WATER

Asthma Symptom Relief

Active Ingredient

HPUS active ingredients

Equal Volumes of each ingredient in 10X, 30X and LM1

Adrenalinum

Antimonium tartaricum

Aralia racemosa

Arsenicum album

Eriodictyon californicum

Eucalyptus globulus

Grindelia

Ipecacuanha

Lobelia inflata

Natrum sulphuricum

Quebracho

Reference image asthma.jpg

Purpose

HPUS active ingredients Purpose

Equal Volumes of each ingredient in 10X, 30X and LM1

Adrenalinum.................................................lung congestion

Antimonium tartaricum..................................shortness of breath

Aralia racemosa...........................................cough, tightness in chest

Arsenicum album.........................................constricted air passages

Eriodictyon californicum................................wheezing, lung pain

Eucalyptus globulus......................................congestion, thick mucus

Grimdelia.....................................................bronchial irritation

Ipecacuanha................................................chest congestion

Lobelia inflata...............................................tightness in chest

Natrum sulphuricum....................................pain from coughing

Quebracho.................................................shortness of breath

Reference image asthma.jpg

Indications and Usage

Uses temporarily relieves symptoms associated with minor asthmatic condition, such as:

- minor shortness of breath
- wheezing
- tightness in chest
- mucus congestion
- bronchial irritation
- pain due to cough

as per various homeopathic Materia Medicas.
Reference image asthma.jpg

Warning

Warnings Asthma can be a life-threatening disease. This product may be used to complement, not replace, standard medical treatment. This product is not intended as a substitute for standard medical care. If you have ever been hospitalized for asthma, consult your physician before using any over-the-counter product to treat symptoms. If symptoms persist or worsen, seek advice of physician. If pregnant or nursing, take only on advice of a healthcare professional. Keep out of reach of children.

Other information

Tamper resistant for your protection. Use only if safety seal is intact.

Reference image asthma.jpg

DOSAGE AND ADMINISTRATION

Directions Initially, depress pump until primed. Hold close to mouth and spray one dose directly into mouth.

Adult Dose 3 pump sprays 3 times per day. Use additionally as needed.

Children 2-12 years 2 pump sprays 3 times per day. Use additionally as needed.

Reference image asthma.jpg

Inactive Ingredient

Bio-Energetically Enhanced taste-free, pure water base.

Reference image asthma.jpg

Keep out of reach of children.

PACKAGE LABEL

King Bio, Inc.

3 Westside Drive

Asheville, NC 28806

www.kingbio.com

Questions call 800-543-3245